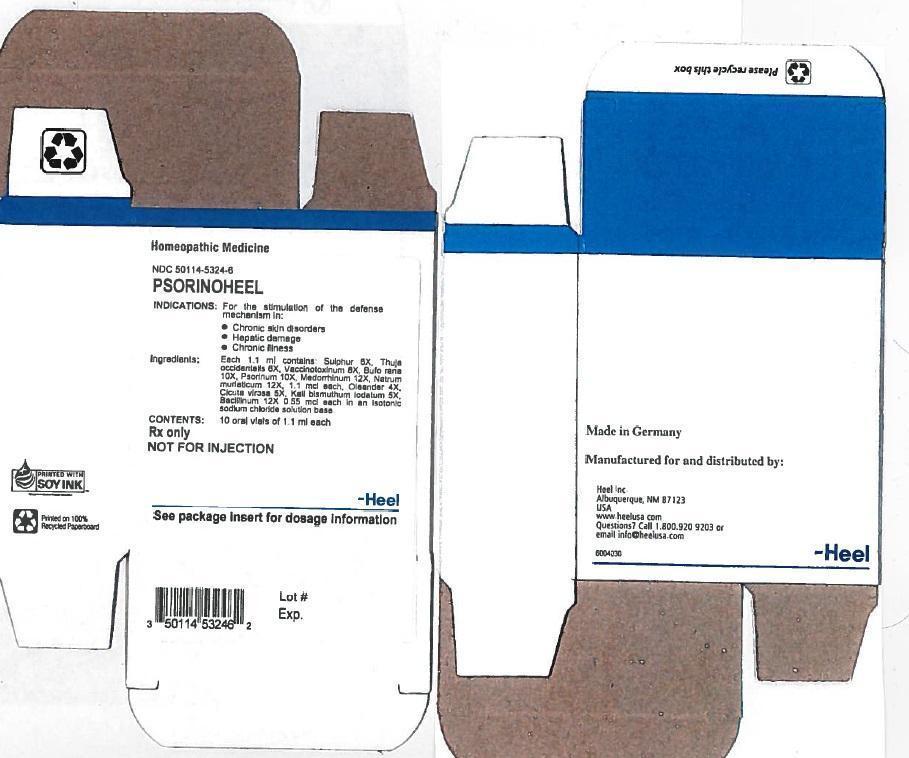 DRUG LABEL: Psorinoheel
NDC: 50114-5324 | Form: SOLUTION
Manufacturer: Heel Inc
Category: homeopathic | Type: HUMAN PRESCRIPTION DRUG LABEL
Date: 20131219

ACTIVE INGREDIENTS: SULFUR 6 [hp_X]/1.1 mL; THUJA OCCIDENTALIS LEAFY TWIG 6 [hp_X]/1.1 mL; VACCINIA VIRUS STRAIN NEW YORK CITY BOARD OF HEALTH LIVE ANTIGEN 8 [hp_X]/1.1 mL; BUFO BUFO CUTANEOUS GLAND 10 [hp_X]/1.1 mL; SCABIES LESION LYSATE (HUMAN) 10 [hp_X]/1.1 mL; GONORRHEAL URETHRAL SECRETION HUMAN 12 [hp_X]/1.1 mL; NERIUM OLEANDER LEAF 4 [hp_X]/1.1 mL; CICUTA VIROSA ROOT 5 [hp_X]/1.1 mL; POTASSIUM DICHROMATE 5 [hp_X]/1.1 mL
INACTIVE INGREDIENTS: SODIUM CHLORIDE

Psorinoheel oral vial

DESCRIPTION

Each1.1 ml ampule contains:

Ingredient Name | Potency | Quantity
Bacillinum | 12x | 0.55µ
Bufo rana | 10x | 1.1µ
Cictuta virosa | 5x | 0.55µ
Kali bismuthum iodatum | 5x | 0.55 µ
Medorrhinum | 12x | 1.1µ
Natrum muriaticum | 12x | 1.1µ
Oleander | 4x | 0.55µ
Psorinum | 10x | 1.1µ
Sulphur | 6x | 1.1µ
Thuja occidentalis | 6x | 1.1µ
Vaccinotoxinum | 8x | 1.1µ

Inactive Ingredient: Isotonic Sodium Chloride solution

INDICATION AND USAGE

Psorinoheel® Oral Vials is a homeopathic drug product indicated for the stimulation of the defense mechanism in chronic skin disorders, hepatic damage , and chronic illness

DOSAGE AND ADMINISTRATION

Dosage:

Adults and children above 6 years: 1 vial orally 1-3 times daily

Children up to 6 years: ½ vial orally 1-3 times daily

CONTRAINDICATIONS

Psorinoheel® Oral Vials are contraindicated in patients with known hypersensitivity to Psorinoheel® or any of its ingredients.

WARNINGS AND PRECAUTIONS

None

ADVERSE REACTIONS

No adverse events have been reported with a causal relationship Psorinoheel® Oral Vials.

OVERDOSAGE

Overdosage: No negative effects of an overdose have been reported and none are expected due to the homeopathic dilutions

CLINICAL PHARMACOLOGY

Mechanism of Action

The exact mechanism of Psorinoheel®Oral Vials is not fully understood.

Pharmacodynamics

Not applicable for homeopathic medicinal products.

DOSAGE

1 oral vial containing 1.1 ml solution for oral administration